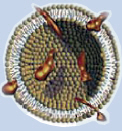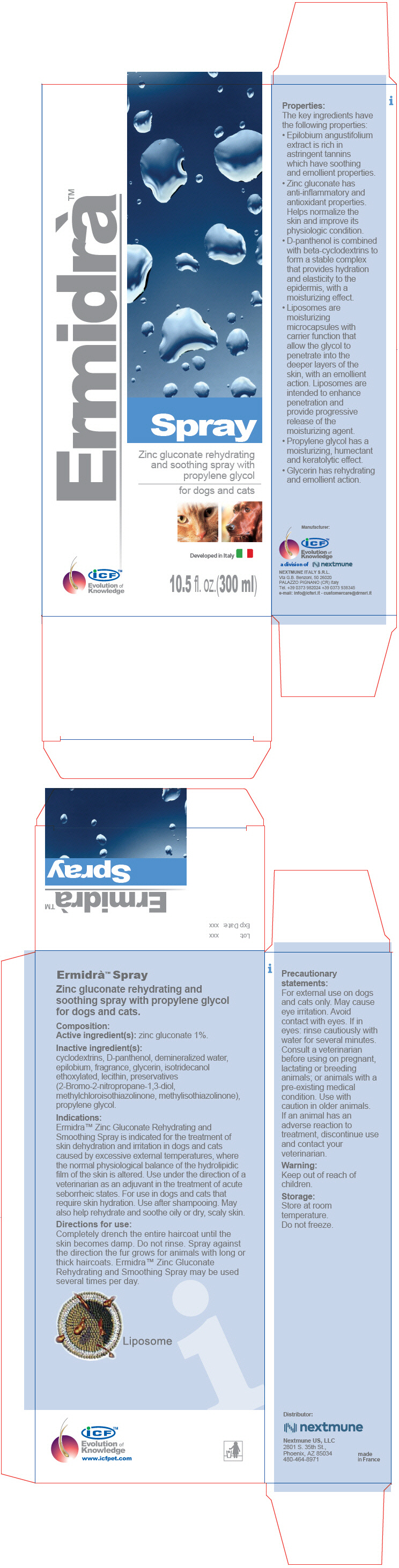 DRUG LABEL: ERMIDRA
NDC: 86127-007 | Form: SPRAY
Manufacturer: Nextmune AB
Category: animal | Type: OTC ANIMAL DRUG LABEL
Date: 20220526

ACTIVE INGREDIENTS: ZINC GLUCONATE 10 mg/1 mL
INACTIVE INGREDIENTS: water; CYCLODEXTRINS; ISOTRIDECYL ALCOHOL; PANTHENOL; PROPYLENE GLYCOL; BRONOPOL; METHYLISOTHIAZOLINONE; METHYLCHLOROISOTHIAZOLINONE; EPILOBIUM ANGUSTIFOLIUM LEAF; LECITHIN, SOYBEAN; GLYCERIN

ERMIDRÀ™ SPRAY

VETERINARY INDICATIONS

Zinc gluconate rehydrating and soothing spray with propylene glycol for dogs and cats.

Composition:

Active ingredient(s): zinc gluconate 1%.

Inactive ingredient(s):

cyclodextrins, D-panthenol, demineralized water, epilobium, fragrance, glycerin, isotridecanol ethoxylated, lecithin, preservatives (2-Bromo-2-nitropropane-1,3-diol, methylchloroisothiazolinone, methylisothiazolinone), propylene glycol.

Indications:

Ermidra™ Zinc Gluconate Rehydrating and Smoothing Spray is indicated for the treatment of skin dehydration and irritation in dogs and cats caused by excessive external temperatures, where the normal physiological balance of the hydrolipidic film of the skin is altered. Use under the direction of a veterinarian as an adjuvant in the treatment of acute seborrheic states. For use in dogs and cats that require skin hydration. Use after shampooing. May also help rehydrate and soothe oily or dry, scaly skin.

Directions for use:

Completely drench the entire haircoat until the skin becomes damp. Do not rinse. Spray against the direction the fur grows for animals with long or thick haircoats. Ermidra™ Zinc Gluconate Rehydrating and Smoothing Spray may be used several times per day.

Liposome

Properties:

The key ingredients have the following properties:

- Epilobium angustifolium extract is rich in astringent tannins which have soothing and emollient properties.
- Zinc gluconate has anti-inflammatory and antioxidant properties. Helps normalize the skin and improve its physiologic condition.
- D-panthenol is combined with beta-cyclodextrins to form a stable complex that provides hydration and elasticity to the epidermis, with a moisturizing effect.
- Liposomes are moisturizing microcapsules with carrier function that allow the glycol to penetrate into the deeper layers of the skin, with an emollient action. Liposomes are intended to enhance penetration and provide progressive release of the moisturizing agent.
- Propylene glycol has a moisturizing, humectant and keratolytic effect.
- Glycerin has rehydrating and emollient action.

Precautionary statements:

For external use on dogs and cats only. May cause eye irritation. Avoid contact with eyes. If in eyes: rinse cautiously with water for several minutes. Consult a veterinarian before using on pregnant, lactating or breeding animals; or animals with a pre-existing medical condition. Use with caution in older animals. If an animal has an adverse reaction to treatment, discontinue use and contact your veterinarian.

Warning:

Keep out of reach of children.

Storage:

Store at room temperature.

Do not freeze.

iCF™
Evolution of
Knowledge
www.icfpet.com

Distributor:

Nextmune US, LLC
2801 S. 35th St.,
Phoenix, AZ 85034
480-464-8971

made
in France

Manufacturer:

iCF™
Evolution of
Knowledge

a division of

NEXTMUNE ITALY S.R.L.
Via G.B. Benzoni, 50 26020
PALAZZO PIGNANO (CR) Italy
Tel. +39 0373 982024 +39 0373 938345
e-mail: info@icfsrl.it - customercare@drnsrl.it

PRINCIPAL DISPLAY PANEL - 300 ml Bottle Carton

Ermidrà™

Spray

Zinc gluconate rehydrating
and soothing spray with
propylene glycol

for dogs and cats

Developed in Italy

iCF™
Evolution of
Knowledge

10.5 fl. oz.(300 ml)